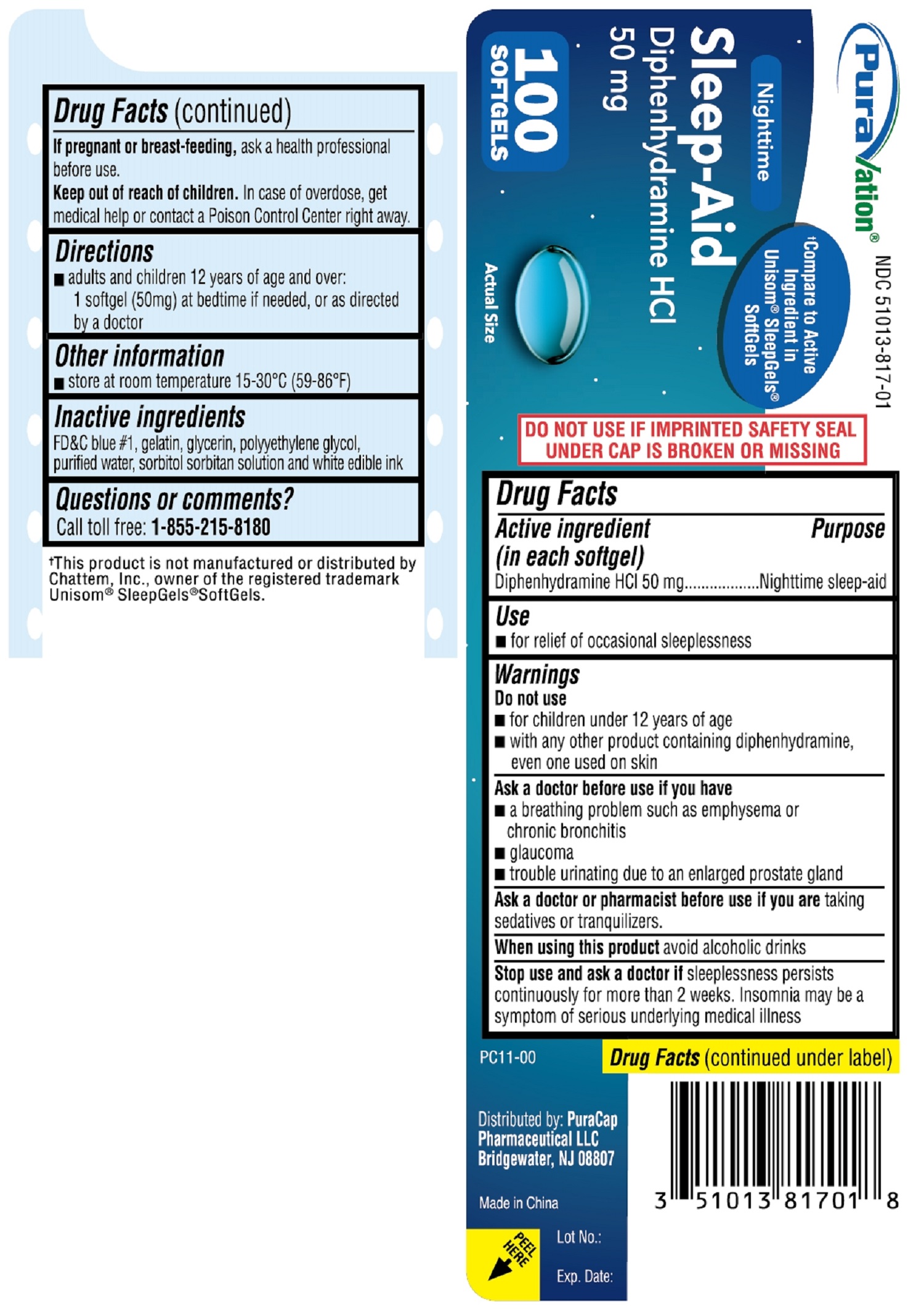 DRUG LABEL: Nighttime SLEEP AID
NDC: 51013-817 | Form: CAPSULE, LIQUID FILLED
Manufacturer: PuraCap Pharmaceutical LLC
Category: otc | Type: HUMAN OTC DRUG LABEL
Date: 20241118

ACTIVE INGREDIENTS: DIPHENHYDRAMINE HYDROCHLORIDE 50 mg/1 1
INACTIVE INGREDIENTS: FD&C BLUE NO. 1; GLYCERIN; GELATIN; SORBITOL; WATER; POLYETHYLENE GLYCOL, UNSPECIFIED

Diphenhydramine HCl 50mg

Drug Facts

Active ingredient (in each softgel)

Diphenhydramine HCl 50 mg

Purpose

Nighttime sleep-aid

Use

- for the relief of occasional sleeplessness

Warnings

Do not use

- for children under 12 years of age
- with any other product containing diphenhydramine, even one used on skin

Ask a doctor before use if you have

- a breathing problem such as emphysema or chronic bronchitis
- glaucoma
- trouble urinating due to enlarged prostate gland

Ask a doctor or pharmacist before use if you are taking sedatives or tranquilizers

When using this product avoid alcoholic drinks

Stop use and ask a doctor if sleeplessness persists continuously for more than 2 weeks. Insomnia may be a symptom of serious underlying medical illness.

PREGNANCY OR BREAST FEEDING

If pregnant or breast-feeding, ask a health professional before use.

Keep out of reach of children.

OVERDOSAGE

In case of overdose, get medical help or contact a Poison Control Center right away.

Directions

- adults and children 12 years of age and over:

1 softgel (50mg) at bedtime if needed, or as directed by a doctor

Other information

- store at room temperature 15°-30° C (59°-86° F)

Inactive ingredients

FD&C blue #1, gelatin, glycerin, polyethylene glycol, purified water, sorbitol sorbitan solution and white edible ink

Questions or comments?

Call toll free: 1-855-215-8180

PRINCIPAL DISPLAY PANEL

Nighttime SLEEP-AID 100 Softgels

Diphenhydramine HCl 50mg

compare to active ingredient in Unisom® SleepGels® SoftGels

NDC 51013-817-01